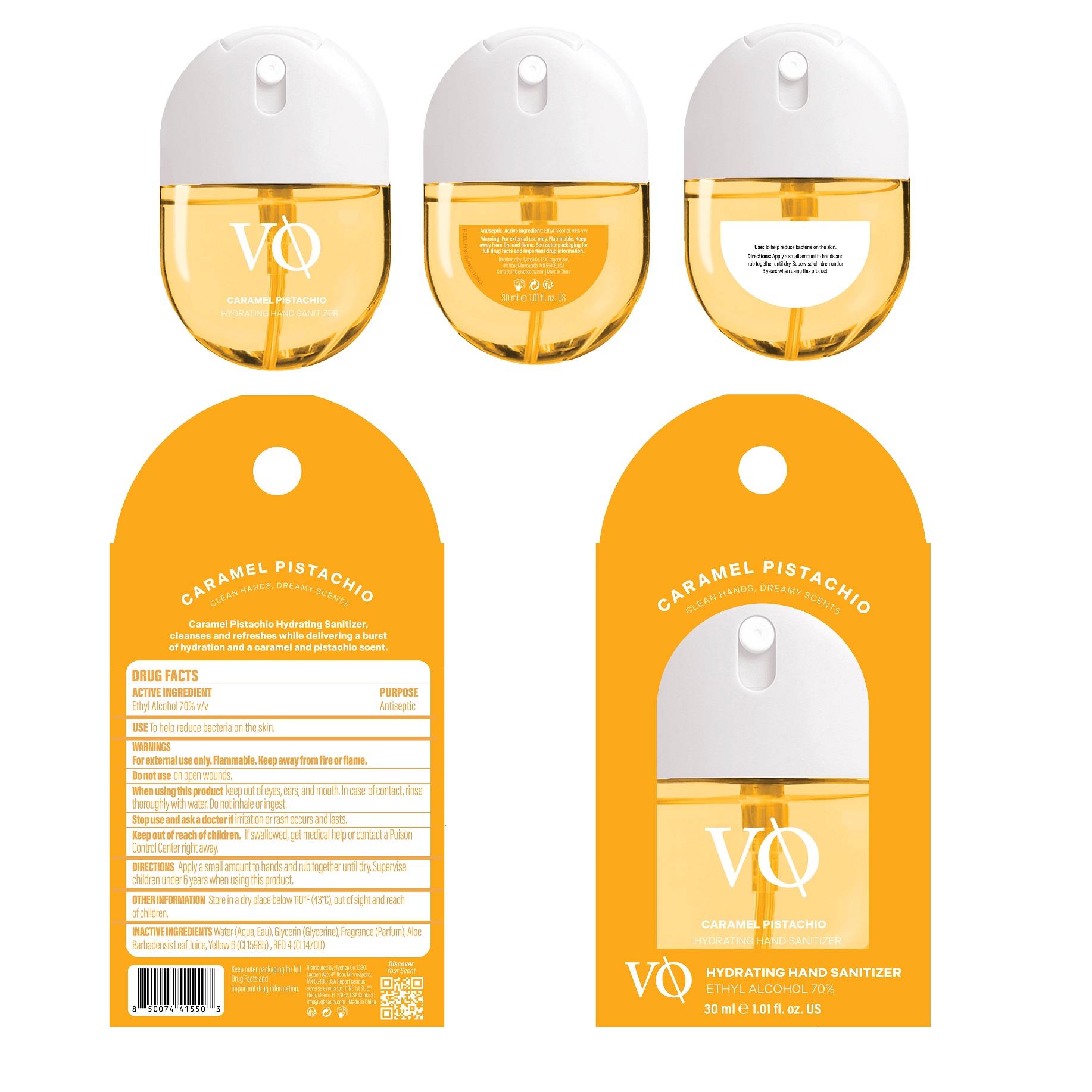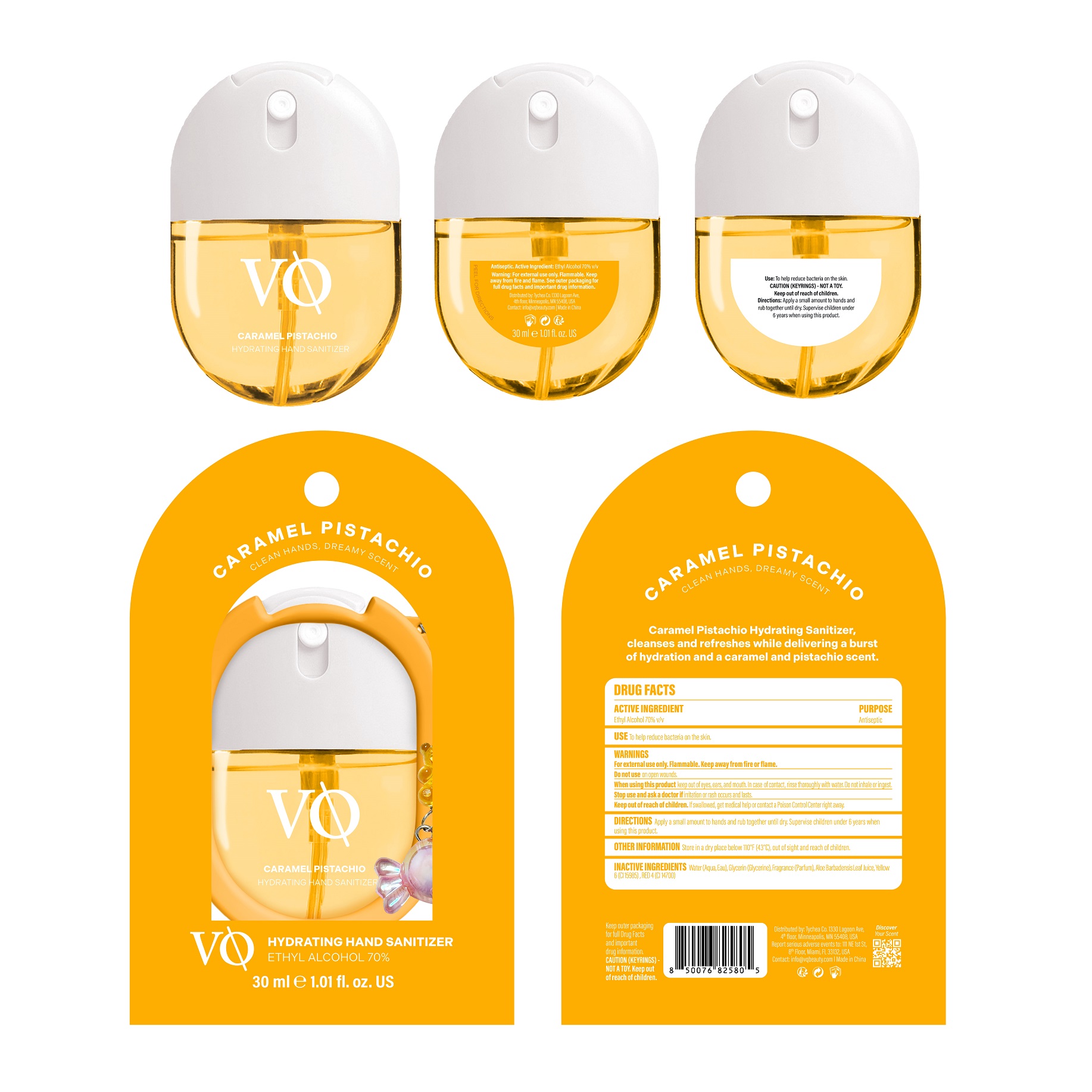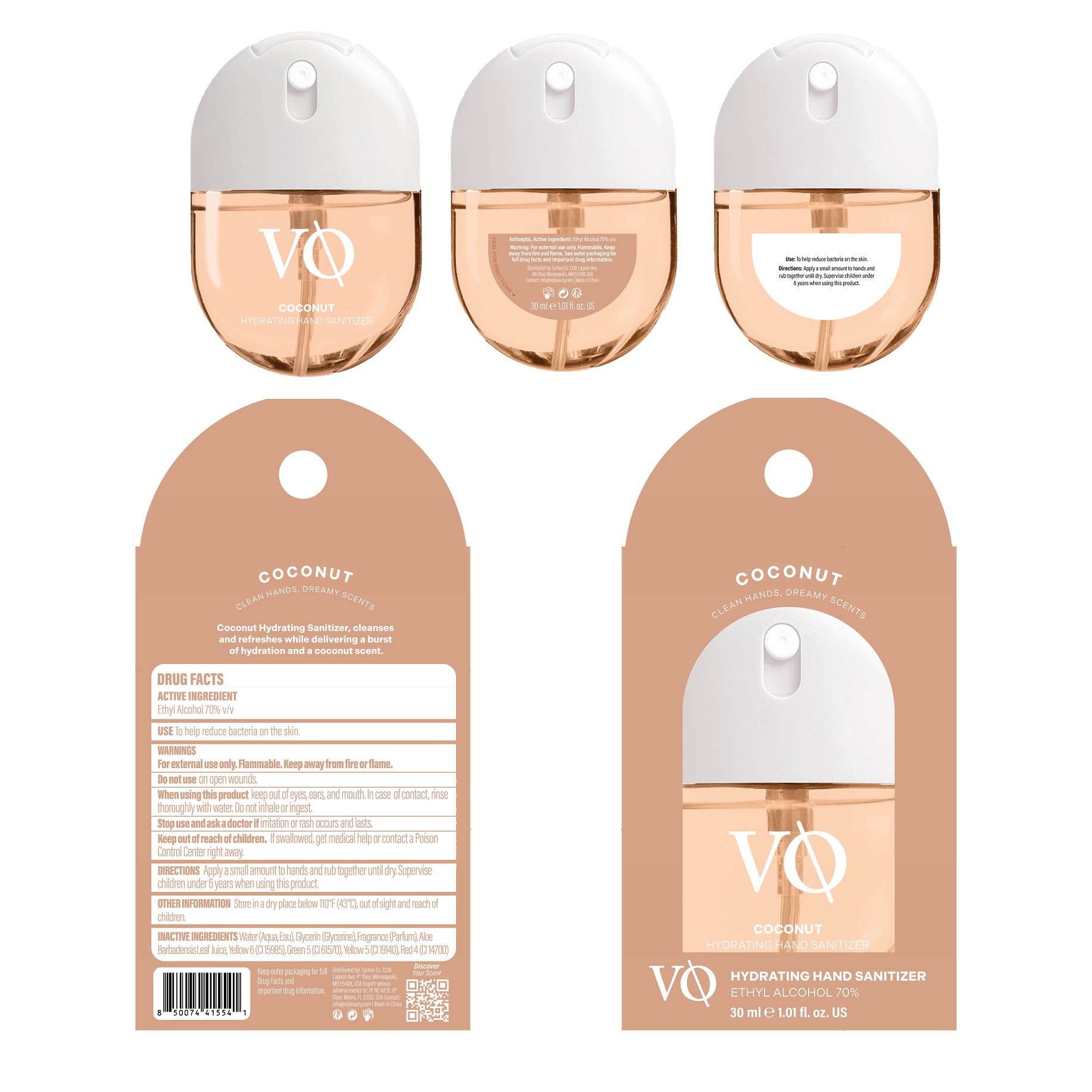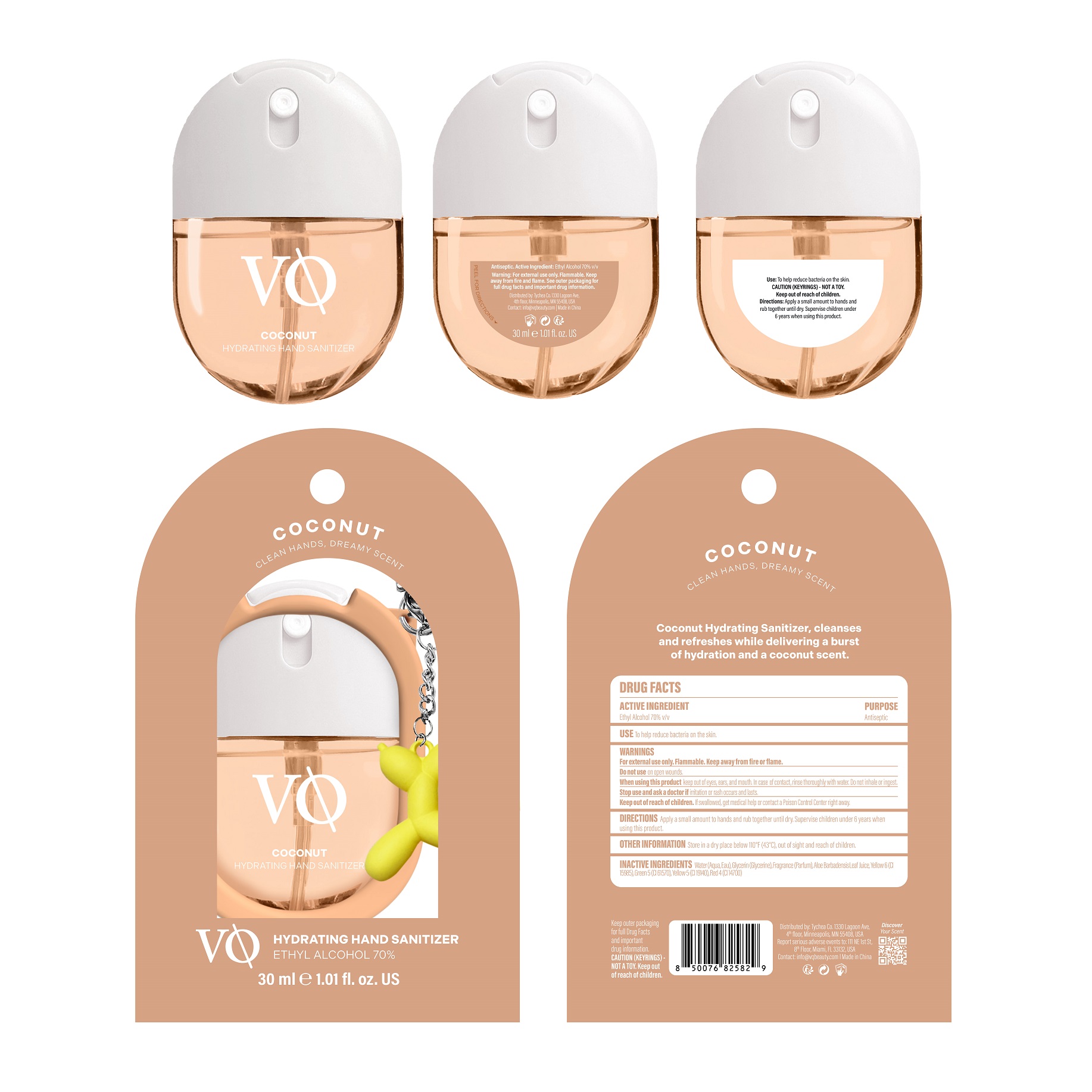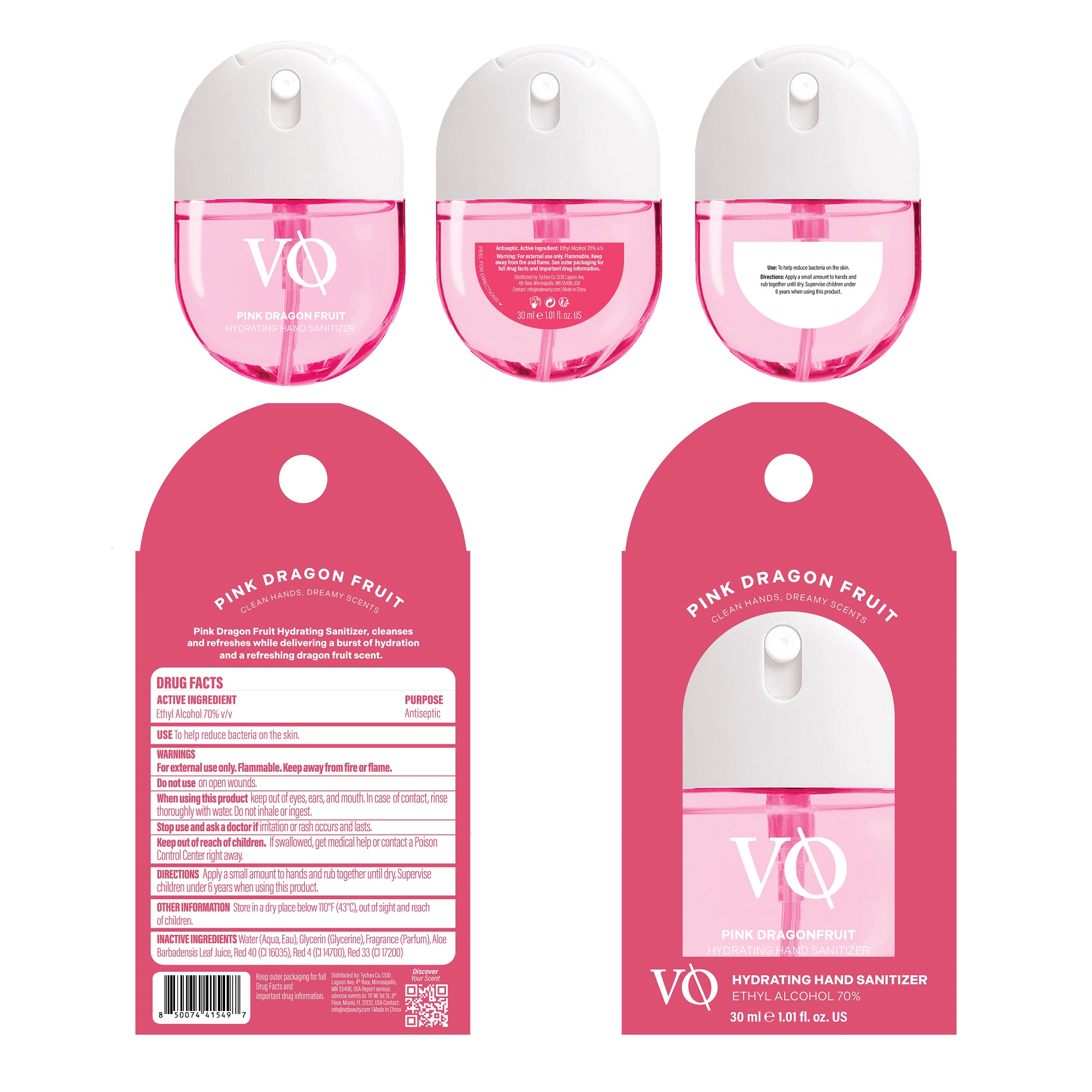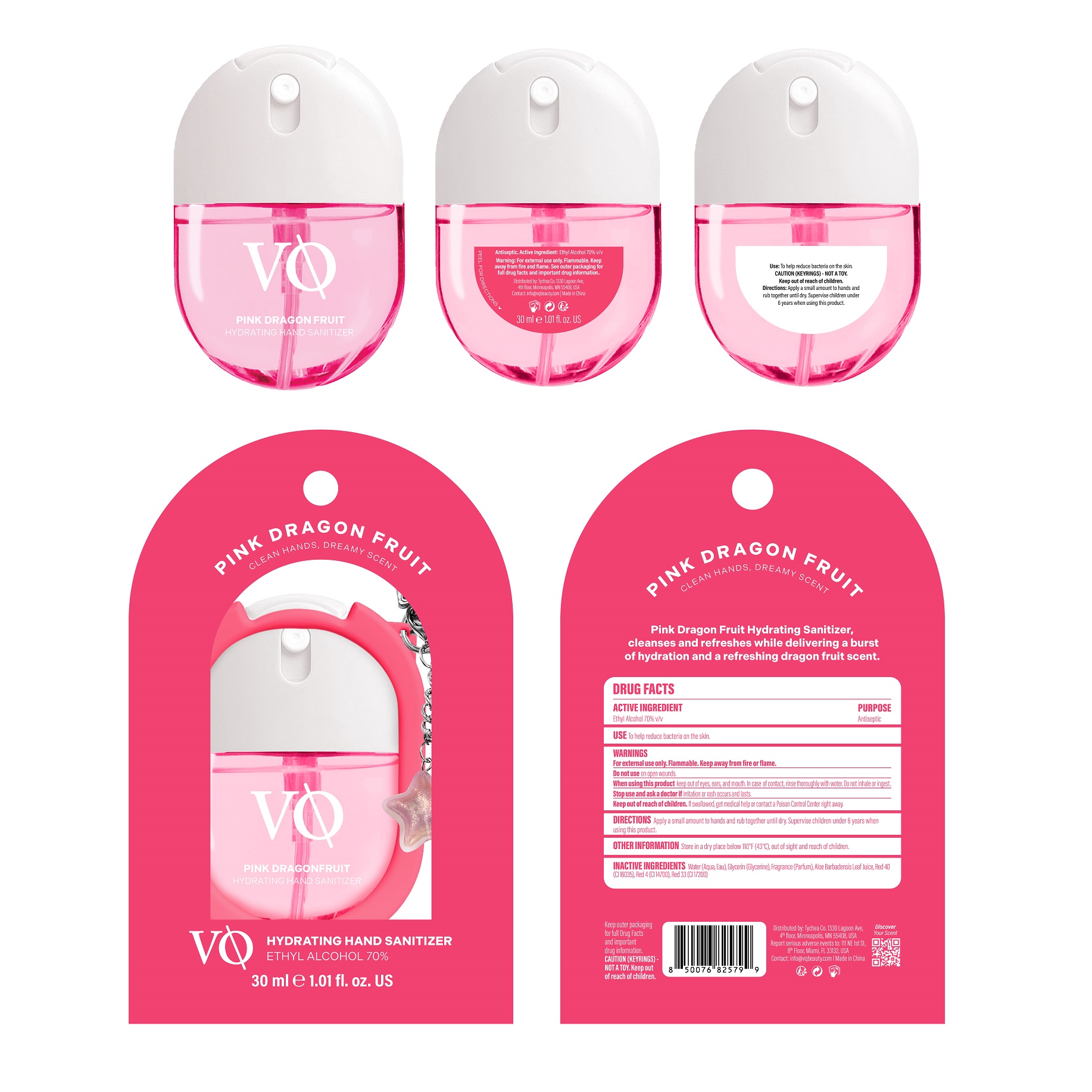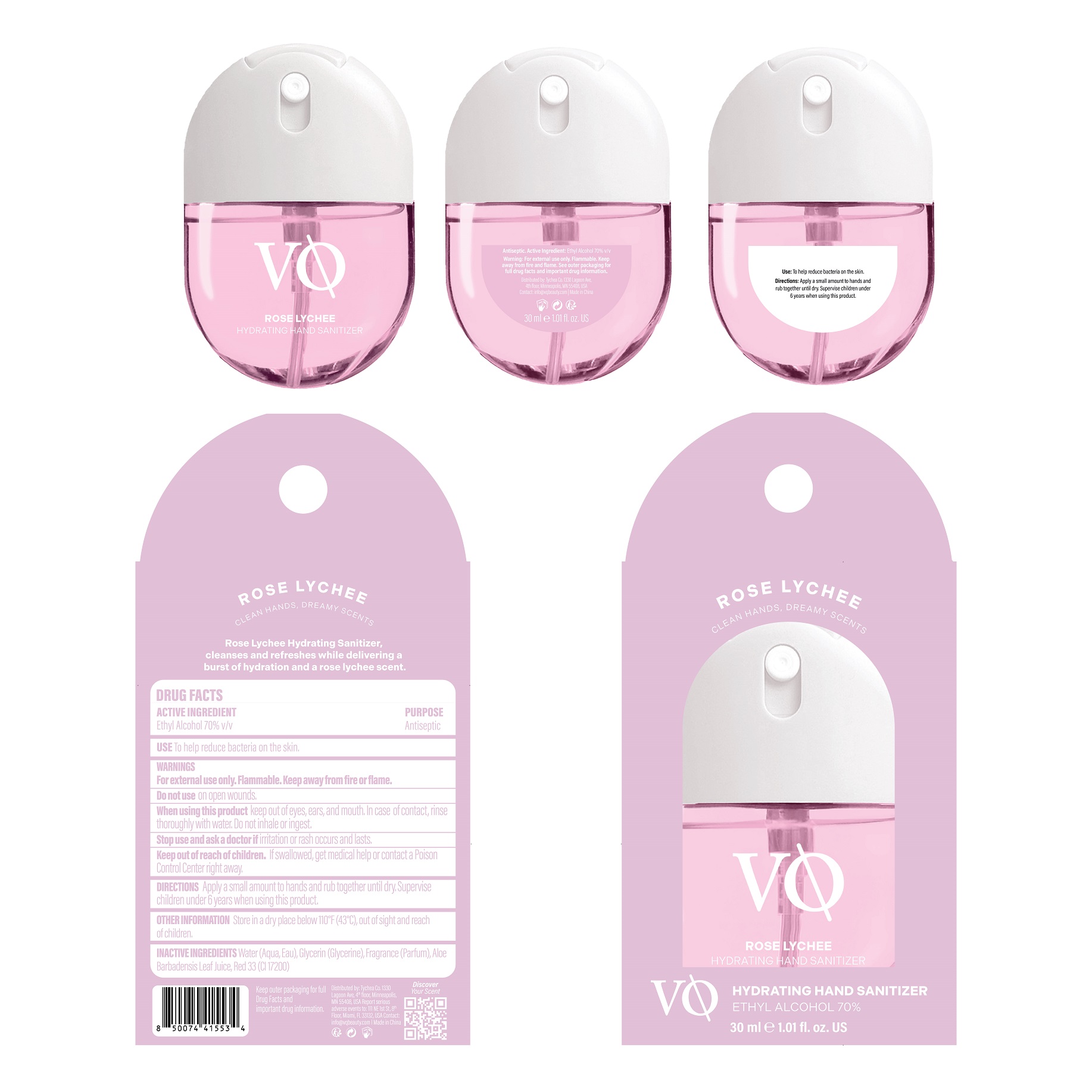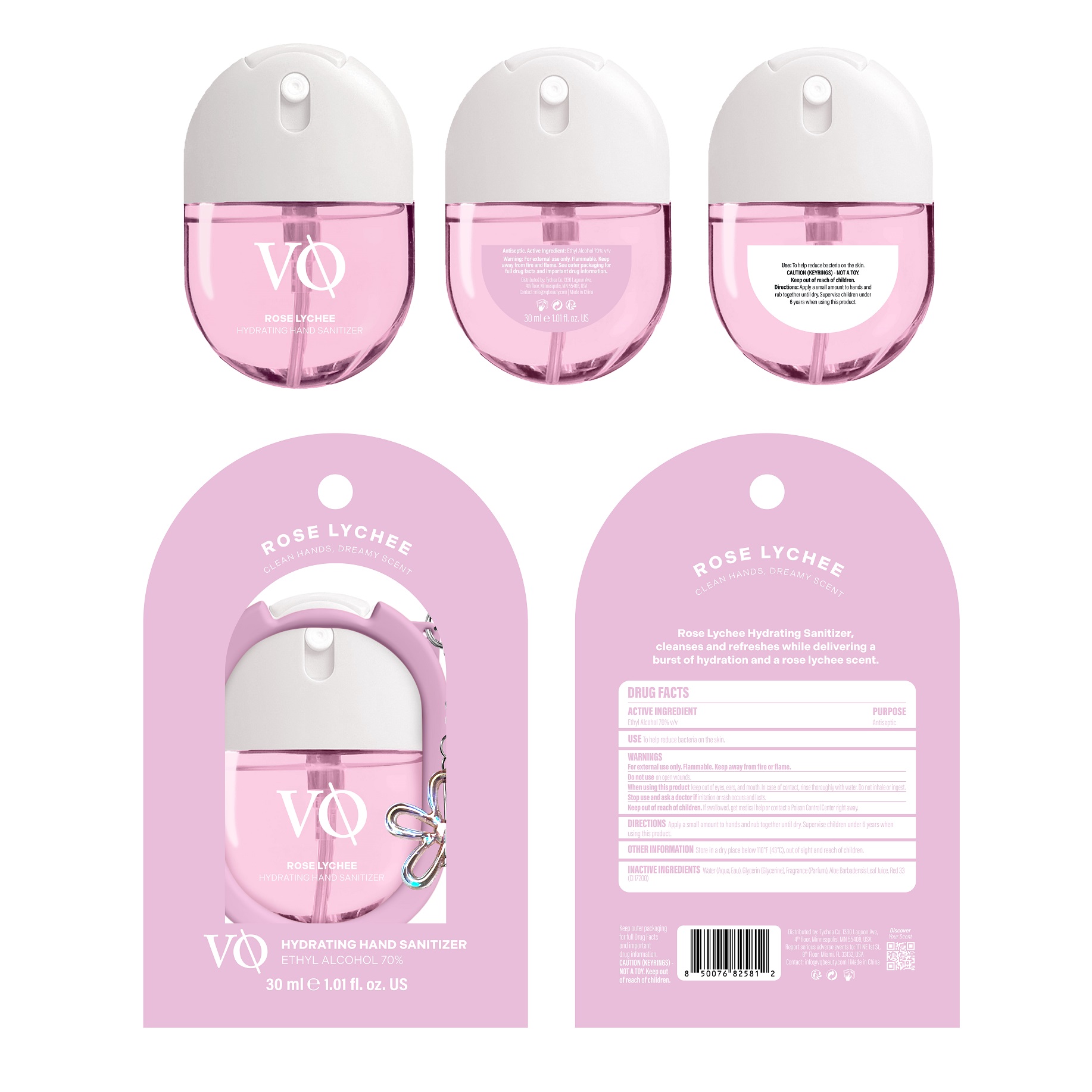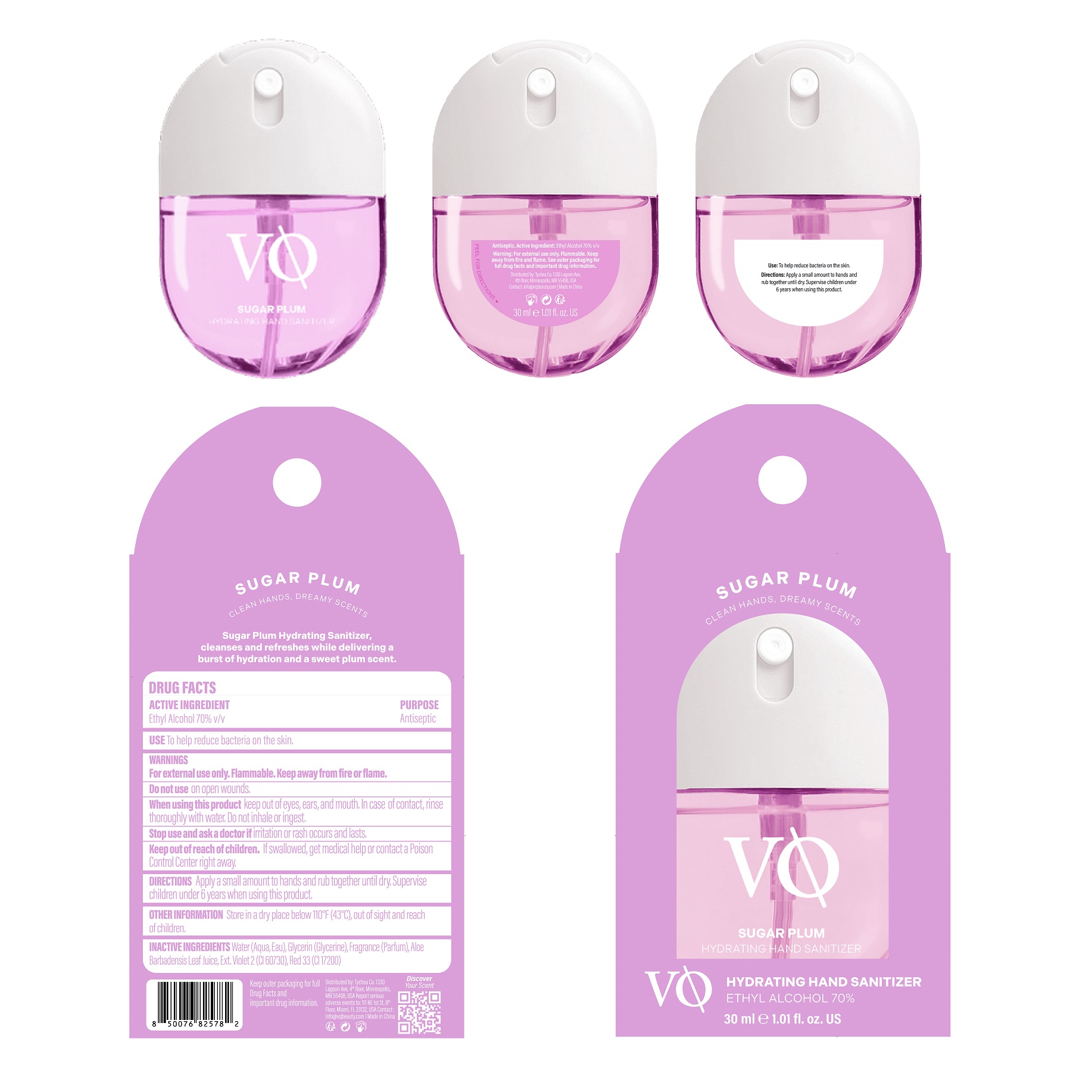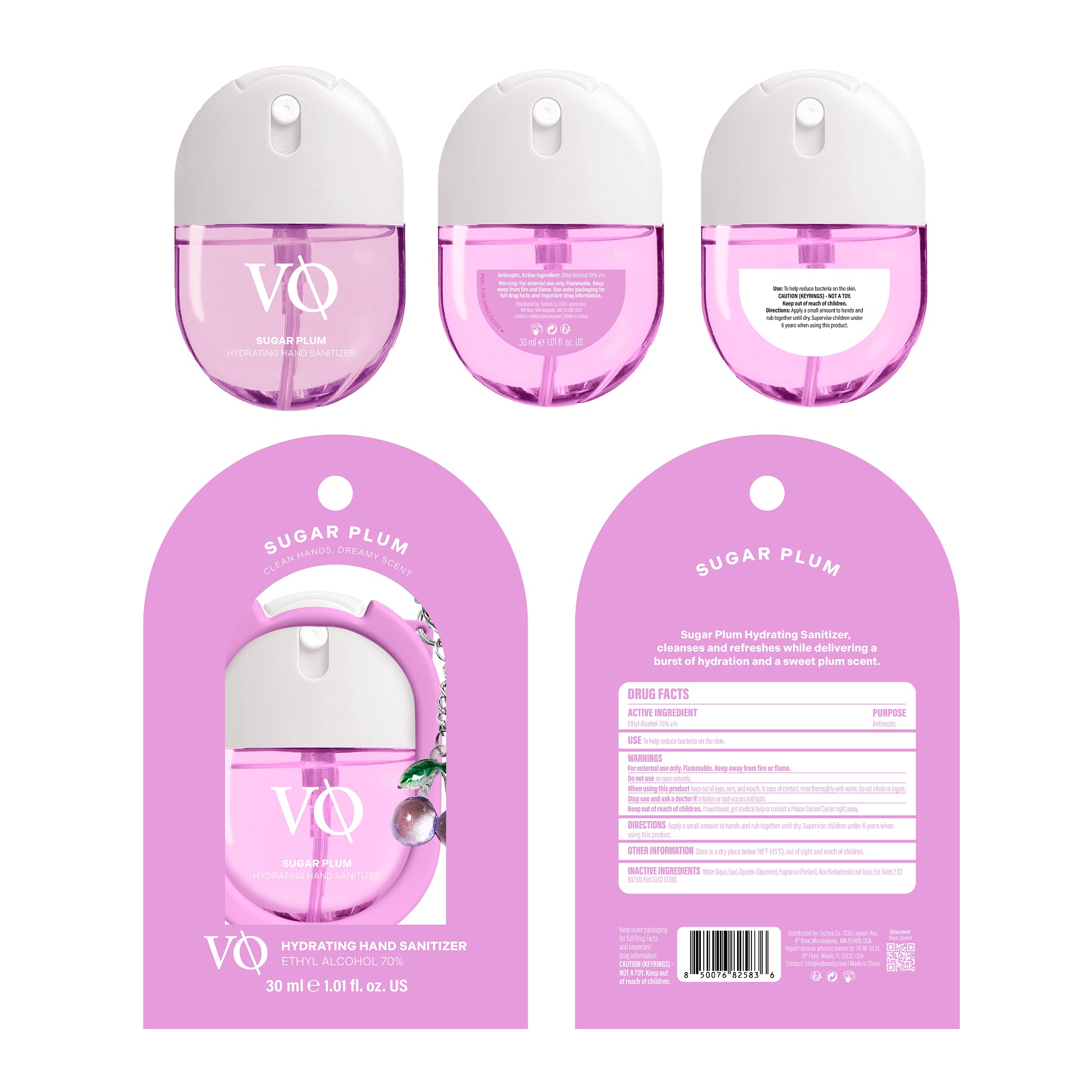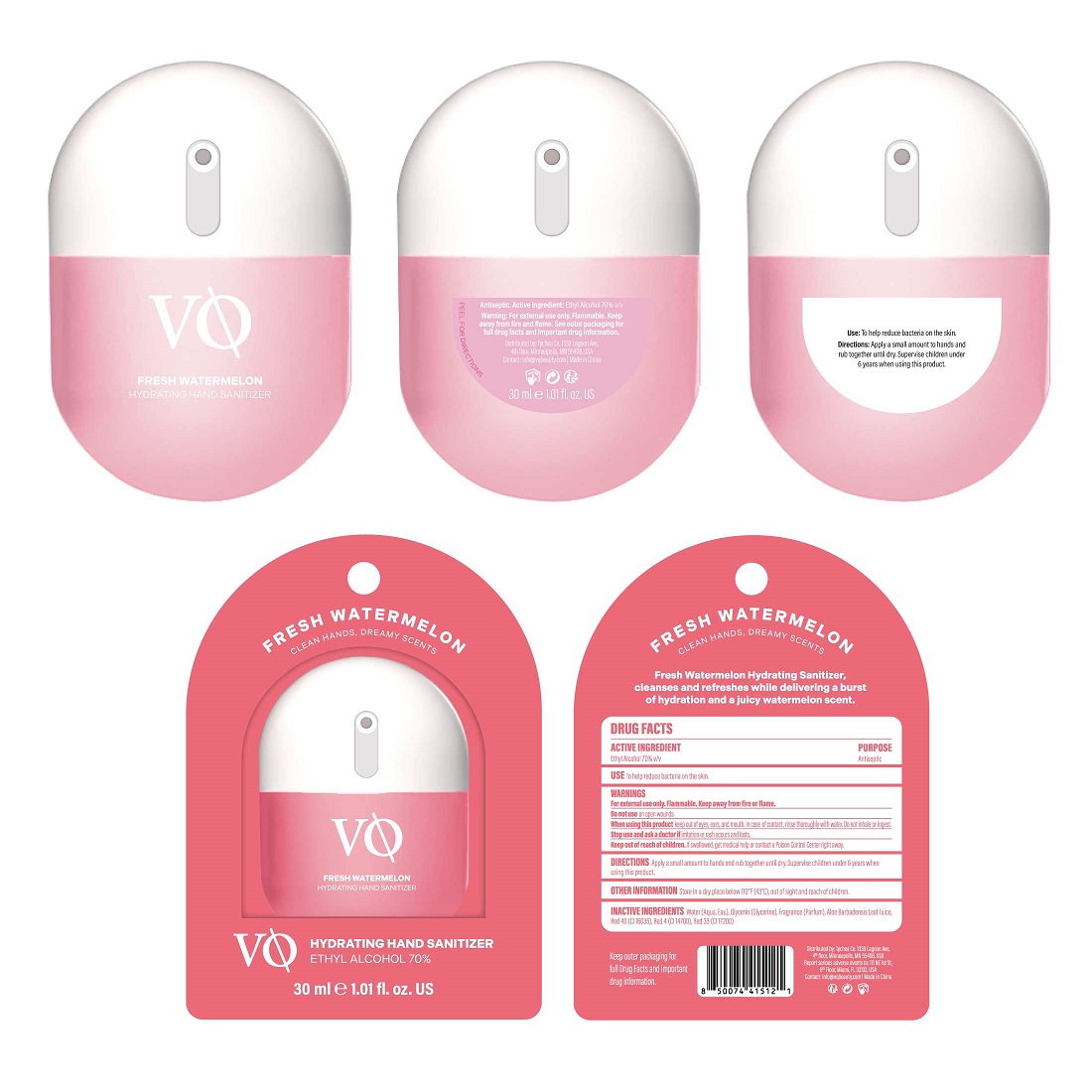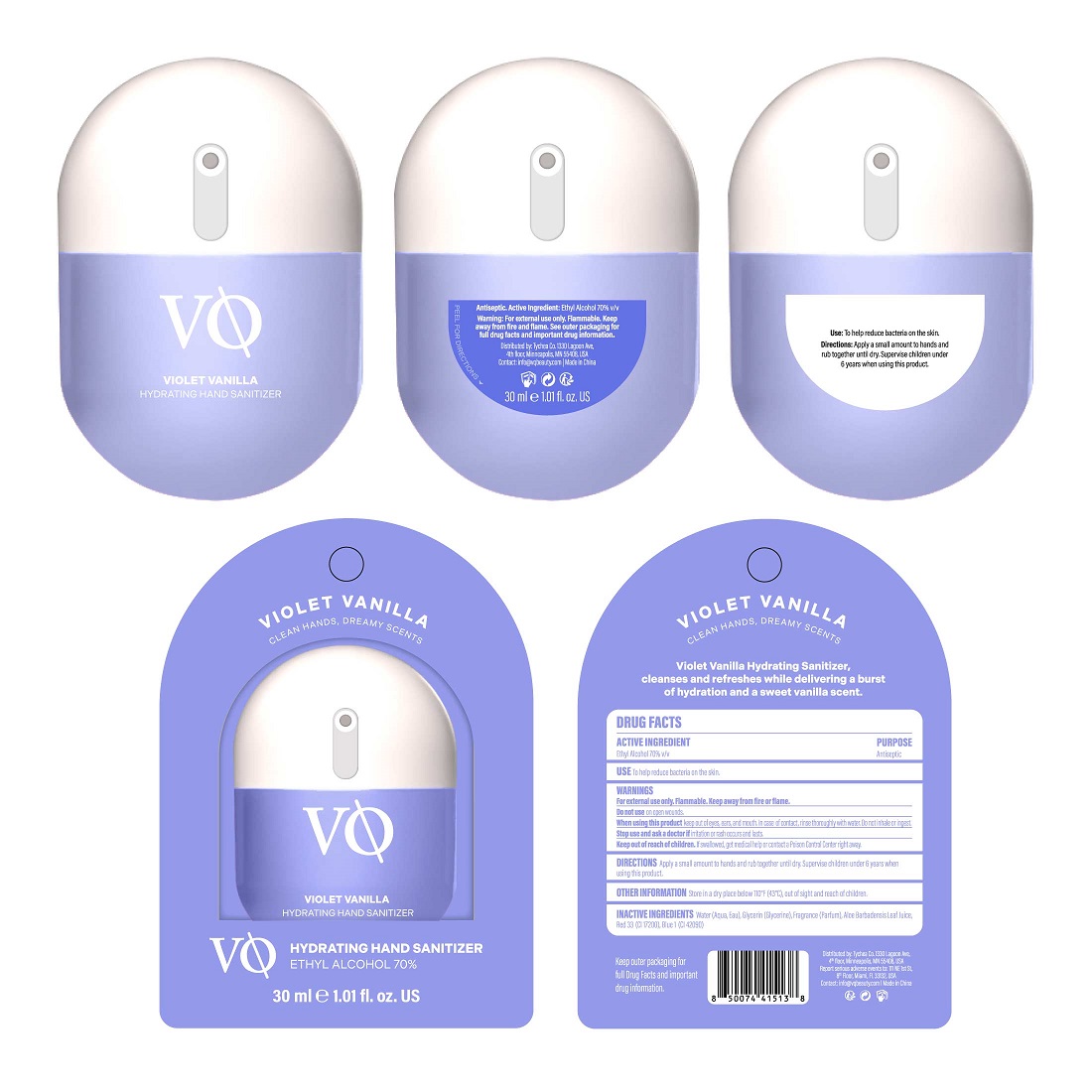 DRUG LABEL: VQ Hydrating Hand Sanitizer
NDC: 85980-002 | Form: LIQUID
Manufacturer: Tychea Co.
Category: otc | Type: HUMAN OTC DRUG LABEL
Date: 20251230

ACTIVE INGREDIENTS: ALCOHOL 70 mL/100 mL
INACTIVE INGREDIENTS: BLUE 1; RED 33; GLYCERIN; WATER; ALOE BARBADENSIS LEAF JUICE

VQ Sanitizer

Active ingredient

Ethyl Alcohol 70% v/v

Purpose

Antiseptic

INDICATIONS AND USAGE

Use To help reduce bacteria on the skin.

Warnings

For external use only. Flammable. Keep away from fire or flame.

Do not use on open wounds.

When using this product keep out of eyes, ears, and mouth. In case of contact, rinse thoroughly with water. Do not inhale or ingest.

Stop use and ask a doctorif irritation or rash occurs and lasts.

Keep out of reach of children. If swallowed, get medical help or contact a Poison Control Center right away.

DOSAGE AND ADMINISTRATION

Directions Apply a small amount to hands and rub together until dry. Supervise children under 6 years when using this product.

Other information

Store in a dry place below 110°F (43°C), out of sight and reach of children.

001 Fresh Watermelon

Inactive ingredients Water (Aqua, Eau), Glycerin (Glycerine), Fragrance (Parfum), Aloe barbadensis Leaf Juice, Red 40 (CI 16035), Red 4 (CI 14700), Red 33 (CI 17200)

002 Violet Vanilla

Inactive ingredients Water (Aqua, Eau), Glycerin (Glycerine), Fragrance (Parfum), Aloe barbadensis Leaf Juice, Red 33 (CI 17200), Blue 1 (CI 42090)

003 Caramel Pistachio

Inactive ingredients Water (Aqua, Eau), Glycerin (Glycerine), Fragrance (Parfum), Aloe barbadensis Leaf Juice, Yellow 6 (CI 15985), Red 4 (CI 14700)

004 Coconut

Inactive ingredients Water (Aqua, Eau), Glycerin (Glycerine), Fragrance (Parfum), Aloe barbadensis Leaf Juice, Yellow 6 (CI 15985), Green 5 (CI 61570), Yellow 5 (CI 19140), Red 4 (CI 14700)

005 Pink Dragon Fruit

Inactive ingredients Water (Aqua, Eau), Glycerin (Glycerine), Fragrance (Parfum), Aloe barbadensis Leaf Juice, Red 40 (CI 16035), Red 4 (CI 14700), Red 33 (CI 17200)

006 Rose Lychee

Inactive ingredients Water (Aqua, Eau), Glycerin (Glycerine), Fragrance (Parfum), Aloe barbadensis Leaf Juice, Red 33 (CI 17200)

007 Sugar Plum

Inactive ingredients Water (Aqua, Eau), Glycerin (Glycerine), Fragrance (Parfum), Aloe barbadensis Leaf Juice, Ext. Violet 2 (CI 60730), Red 33 (CI 17200)

Keep outer packaging for full Drug Facts and important drug information.

Distributed by: Tychea Co. 1330 Lagoon Ave, 4th floor, Minneapolis, MN 55408, USA

Report serious adverse events to: 111 NE 1st St, 8th Floor, Miami, FL 33132, USA

Contact: info@vqbeauty.com | Made in China

001 Fresh Watermelon

FRESH WATERMELON

CLEAN HANDS, DREAMY SCENTS

VO

FRESH WATERMELON

HYDRATING HAND SANITIZER

ETHYL ALCOHOL 70%

30 ml ℮ 1.01 fl. oz. US

002 Violet vanilla

VIOLET VANILLA

CLEAN HANDS, DREAMY SCENTS

VO

VIOLET VANILLA

HYDRATING HAND SANITIZER

ETHYL ALCOHOL 70%

30 ml ℮ 1.01 fl. oz. US